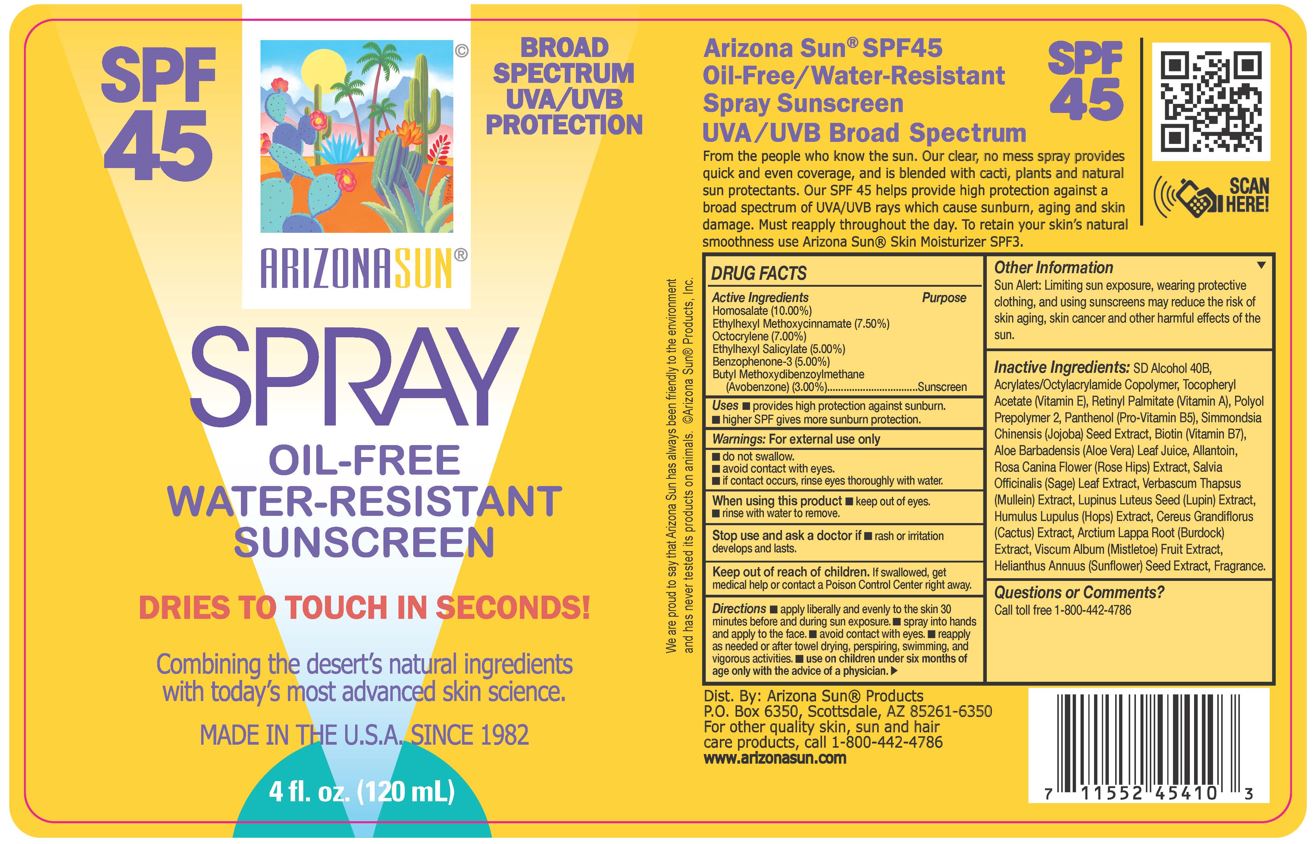 DRUG LABEL: Arizona Sun SPF 45 Sunscreen
NDC: 61973-108 | Form: SPRAY
Manufacturer: Arizona Sun Products
Category: otc | Type: HUMAN OTC DRUG LABEL
Date: 20240220

ACTIVE INGREDIENTS: OCTOCRYLENE 70 mg/1 g; OXYBENZONE 50 mg/1 g; AVOBENZONE 30 mg/1 g; OCTISALATE 50 mg/1 g; HOMOSALATE 100 mg/1 g; OCTINOXATE 50 mg/1 g
INACTIVE INGREDIENTS: ALCOHOL; BIOTIN; ALOE VERA LEAF; SAGE; LUPINUS LUTEUS SEED; HOPS; VISCUM ALBUM FRUIT; ROSA CANINA FLOWER; SIMMONDSIA CHINENSIS SEED; ARCTIUM LAPPA ROOT; .ALPHA.-TOCOPHEROL ACETATE; SUNFLOWER SEED; PANTHENOL; PPG-12/SMDI COPOLYMER; ALLANTOIN; MULLEIN LEAF; ACRYLATE/ISOBUTYL METHACRYLATE/N-TERT-OCTYLACRYLAMIDE COPOLYMER (40000 MW); VITAMIN A PALMITATE; SELENICEREUS GRANDIFLORUS FLOWER

SPF 45 Spray

Active Ingredients

Homosalate (10.00%), Ethylhexyl Methoxycinnamate (7.50%), Octocrylene (7.00%), Ethylhexyl Salicylate (5.00%), Benzophenone-3 (5.00%), Butyl Methoxydibenzoylmethane (Avobenzone) (3.00%)

Purpose

Sunscreen

Uses

Provides high sunburn protection. Higher SPF gives more sunburn protection

Warnings

For external use only. Do not swallow. Avoid contact with eyes. If contact occurs, rinse eyes thoroughly with water.

When using this product

keep out of eyes. Rinse with water to remove.

Stop and ask a doctor if

rash or irritation develops and lasts.

Keep out of the reach of children.

If swallowed get medical help or contact a poison control center right away.

Directions

Apply liberally and evenly to the skin 30 minutes before and during sun exposure. Spray into hands and apply to the face. Avoid contact with eyes. Reapply as needed or after towel drying, perspiring, swimming, and vigorous activities. Use on children under six months of age only wih the advise of a physician.

Other Information

Sun Alert: Limiting sun exposure, wearing protective clothing, and using suscreen may reduce the risk of skin aging, skin cancer and other harmful effects of the sun.

Inactive Ingredients

SD Alcohol 40B, Acrylates/ Octylacrylamide Copolymer, Tocopheryl Acetate (Vitamin E), Retinyl Palmitate, Polyol Prepolymer 2, Panthenol, Simmondsia Chinensis (Jojoba) Seed Extract, Biotin, Aloe Barbadensis (Aloe Vera) Leaf Juice, Allantoin, Rosa Canina Flower (Rose Hips) Extract, Salvia Officinalis (Sage) Leaf Extract, Verbascum Thapsus (Mullein) Extract, Lupinus Luteus Seed (Lupin) Extract, Humulus Lupulus (Hops) Extract, Cereus Grandiflorus (Cactus) Extract, Arctium Lappa Root (Burdock) Extract, Viscum Album (Mistletoe) Fruit Extract, Helianthus Annuus (Sunflower) Seed Extract, Fragrance

Questions or Comments?

Call toll free 1-800-442-4786